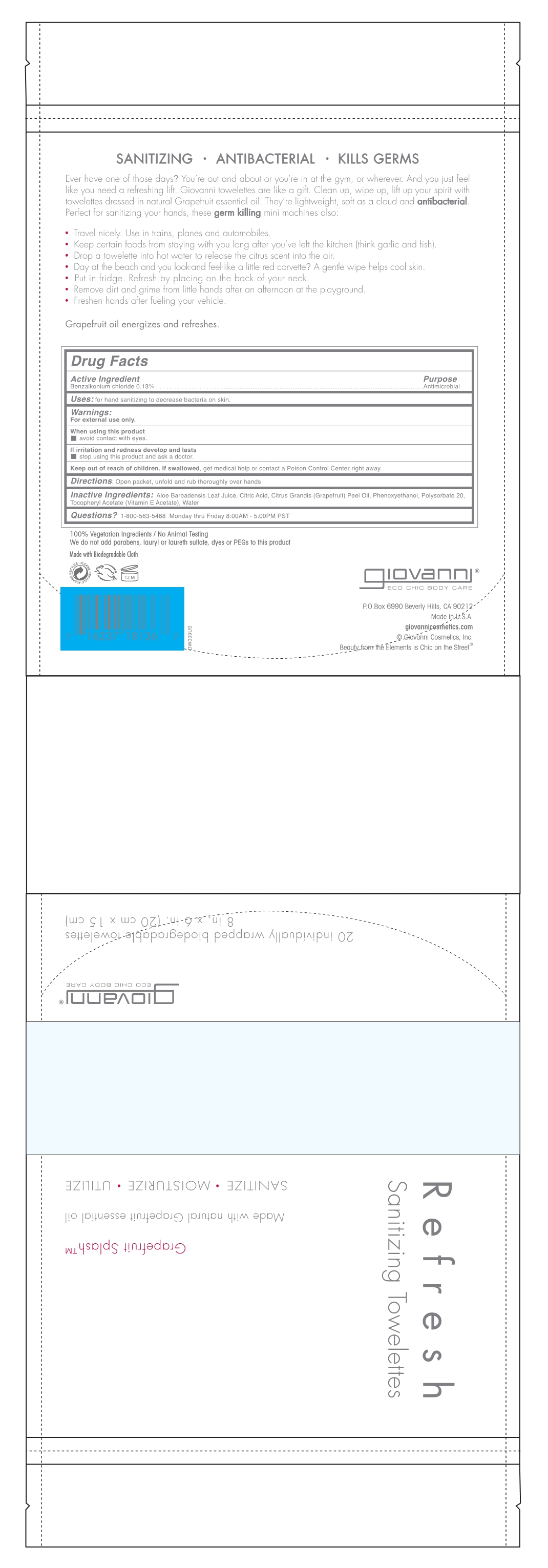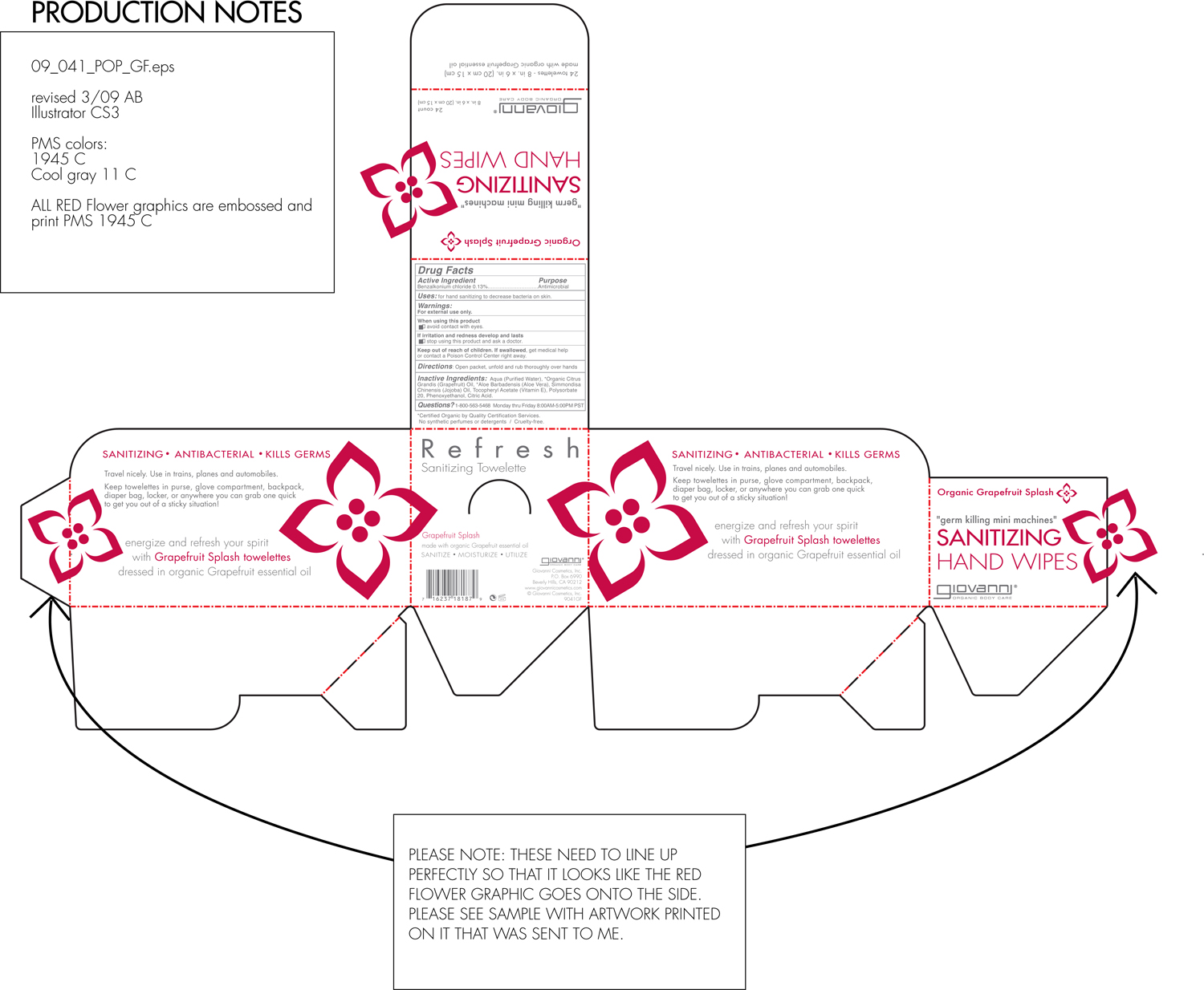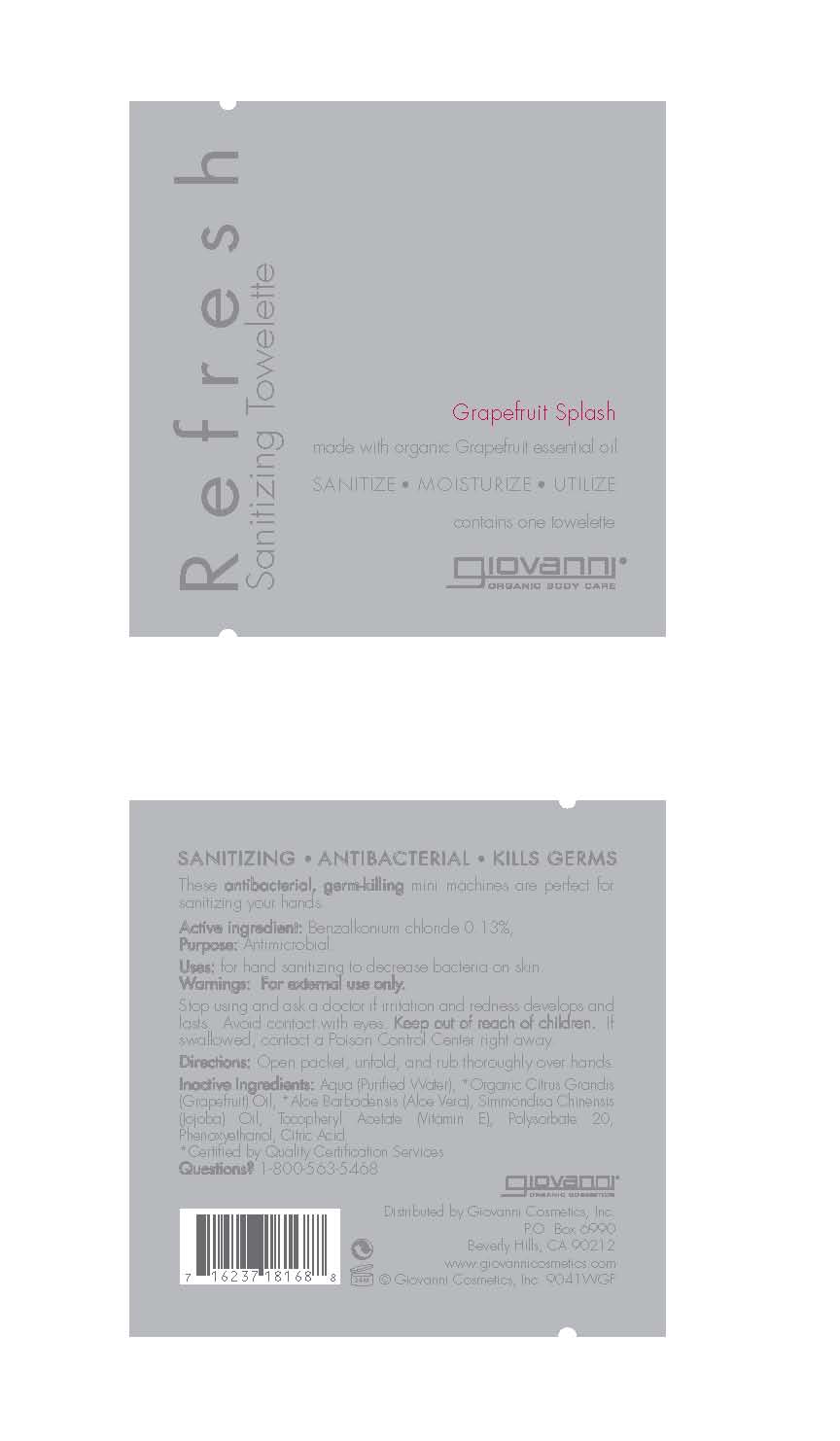 DRUG LABEL: Refresh Sanitizing Towlette
NDC: 45942-1629 | Form: LIQUID
Manufacturer: GIOVANNI COSMETICS INC
Category: otc | Type: HUMAN OTC DRUG LABEL
Date: 20180129

ACTIVE INGREDIENTS: BENZALKONIUM CHLORIDE 0.13 g/100 mL
INACTIVE INGREDIENTS: Water; Grapefruit; Polysorbate 20; .ALPHA.-TOCOPHEROL ACETATE, DL-; Aloe Vera Leaf; Phenoxyethanol; ANHYDROUS CITRIC ACID

Refresh Packaging

Active ingredient

Benzalkonium Chloride 0.13%

Purpose

Antimicrobial

Uses: For hand sanitizing to decrease bacteria on skin.

Uses

For hand sanitizing to decrease bacteria on the skin.

Directions

Open packet, unfold, and rub thoroughly over hands

Keep out of reach of children

If swallowed, get medical help or contact a Poison Control Center right away.

Directions

Open packet, unfold and rub thoroughly over hands.

Inactive ingredients

Aloe Barbadensis Leaf Juice, Citric Acid, Citrus Grandis (Grapefruit) Peel Oil, Phenoxyethanol, Polysorbate 20, Tocopheryl Acetate (Vitamin E Acetate), Water

Warnings

For external use only.
When using this product avoid contact with eyes.
If irritation and redness develop and lasts, stop using this product and ask a doctor.

Questions

1-800-563-5458 Monday thru Friday 8:00 AM - 5:00 PM PST

PACKAGE LABEL

Refresh Sanitizing Towelettes

Grapefruit Splash

Made with organic grapefruit essential oil.